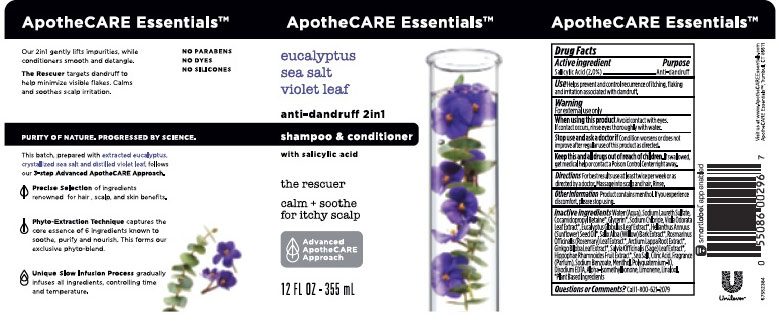 DRUG LABEL: ApotheCare
NDC: 64942-1627 | Form: LIQUID
Manufacturer: Conopco, Inc. d/b/a/ Unilever
Category: otc | Type: HUMAN OTC DRUG LABEL
Date: 20221207

ACTIVE INGREDIENTS: SALICYLIC ACID 2 g/100 mL
INACTIVE INGREDIENTS: WATER; SODIUM LAURETH-3 SULFATE; COCAMIDOPROPYL BETAINE; SODIUM CHLORIDE; SUNFLOWER OIL; GLYCERIN; ARCTIUM LAPPA ROOT; GINKGO; SEA SALT; CITRIC ACID MONOHYDRATE; SODIUM BENZOATE; MENTHOL; POLYQUATERNIUM-10 (1000 MPA.S AT 2%); EDETATE DISODIUM; ISOMETHYL-.ALPHA.-IONONE; LIMONENE, (+)-; LINALOOL, (+/-)-

ApotheCare Essentials Eucalyptus Sea Salt Violet Leaf 2in1 Anti-Dandruff Shampoo & Conditioner

APOTHECARE ESSENTIALS EUCALYPTUS SEA SALT VIOLET LEAF 2IN1 ANTI-DANDRUFF SHAMPOO & CONDITIONER - salicylic acid emulsion

ApotheCare Essentials Eucalyptus Sea Salt Violet Leaf 2in1 Anti-Dandruff Shampoo & Conditioner

Drug Facts

Active ingredient
Salicylic Acid (2.0%)

Purpose

Anti-dandruff

Use

Helps prevent and control recurrence of itching, flaking and irritation associated with dandruff.

Warnings

For external use only
When using this product Avoid contact with eyes. If contact occurs, rinse eyes thoroughly with water.
Stop use and ask a doctor if Condition worsens or does not improve after regular use of this product as directed.

KEEP OUT OF REACH OF CHILDREN

Keep this and all drugs out of reach of children. If swallowed, get medical help or contact a Poison Control Center right away.

Directions

For best results use at least twice per week or as directed by a doctor. Massage into scalp and hair. Rinse.

Other Information

Product contains menthol. If you experience discomfort, please stop using.

Inactive Ingredients

Water (Aqua), Sodium Laureth Sulfate, Cocamidopropyl Betaine, Glycerin, Sodium Chloride, Viola Odorata Leaf Extract, Eucalyptus Globulus Leaf Extract, Helianthus Annuus (Sunflower) Seed Oil, Salix Alba (Willow) Bark Extract, Rosmarinus Officinalis (Rosemary) Leaf Extract, Arctium Lappa Root Extract,Ginkgo Biloba Leaf Extract, Salvia Officinalis (Sage) Leaf Extract, Hippophae Rhamnoides Fruit Extract, Sea Salt, Citric Acid, Fragrance (Parfum), Sodium Benzoate, Menthol, Polyquaternium-10, Disodium EDTA, Alpha-Isomethyl Ionone, Limonene, Linalool.

Questions, comments?

Call 1-800-761-3683